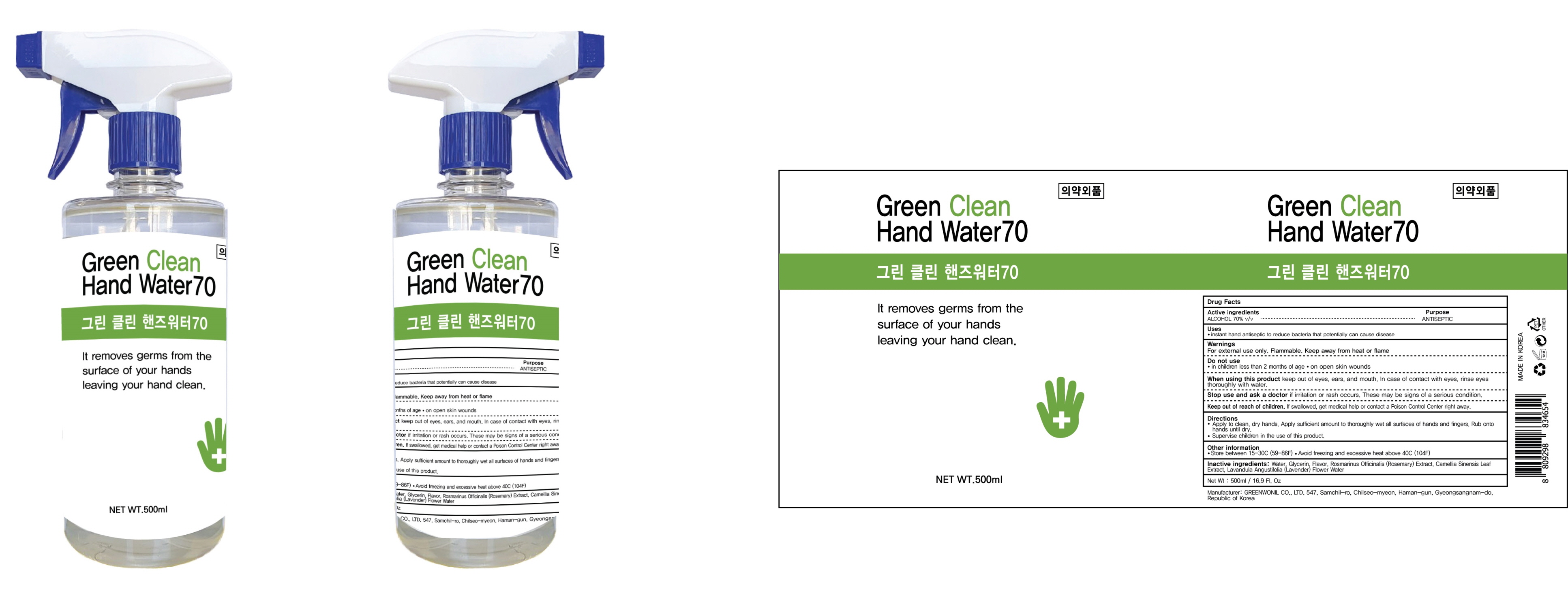 DRUG LABEL: Green Clean Hand Water 70
NDC: 76532-060 | Form: SPRAY
Manufacturer: GREEN WONIL CO., LTD.
Category: otc | Type: HUMAN OTC DRUG LABEL
Date: 20200616

ACTIVE INGREDIENTS: ALCOHOL 350 mL/500 mL
INACTIVE INGREDIENTS: Water; Glycerin; ROSEMARY; GREEN TEA LEAF; LAVENDER OIL

ACTIVE INGREDIENT

ALCOHOL 70% v/v

INACTIVE INGREDIENT

Water, Glycerin, Flavor, Rosmarinus Officinalis (Rosemary) Extract, Camellia Sinensis Leaf Extract, Lavandula Angustifolia (Lavender) Flower Water

PURPOSE

ANTISEPTIC

WARNINGS

For external use only. Flammable. Keep away from heat or flame

--------------------------------------------------------------------------------------------------------
Do not use
• in children less than 2 months of age
• on open skin wounds
--------------------------------------------------------------------------------------------------------
When using this product keep out of eyes, ears, and mouth. In case of contact with eyes, rinse eyes thoroughly with water.
--------------------------------------------------------------------------------------------------------
Stop use and ask a doctor if irritation or rash occurs. These may be signs of a serious condition.

KEEP OUT OF REACH OF CHILDREN

If swallowed, get medical help or contact a Poison Control Center right away.

Uses

• instant hand antiseptic to reduce bacteria that potentially can cause disease

Directions

• Apply to clean, dry hands. Apply sufficient amount to thoroughly wet all surfaces of hands and fingers. Rub onto hands until dry.
• Supervise children in the use of this product.

Other Information

• Store between 15-30C (59-86F)

• Avoid freezing and excessive heat above 40C (104F)